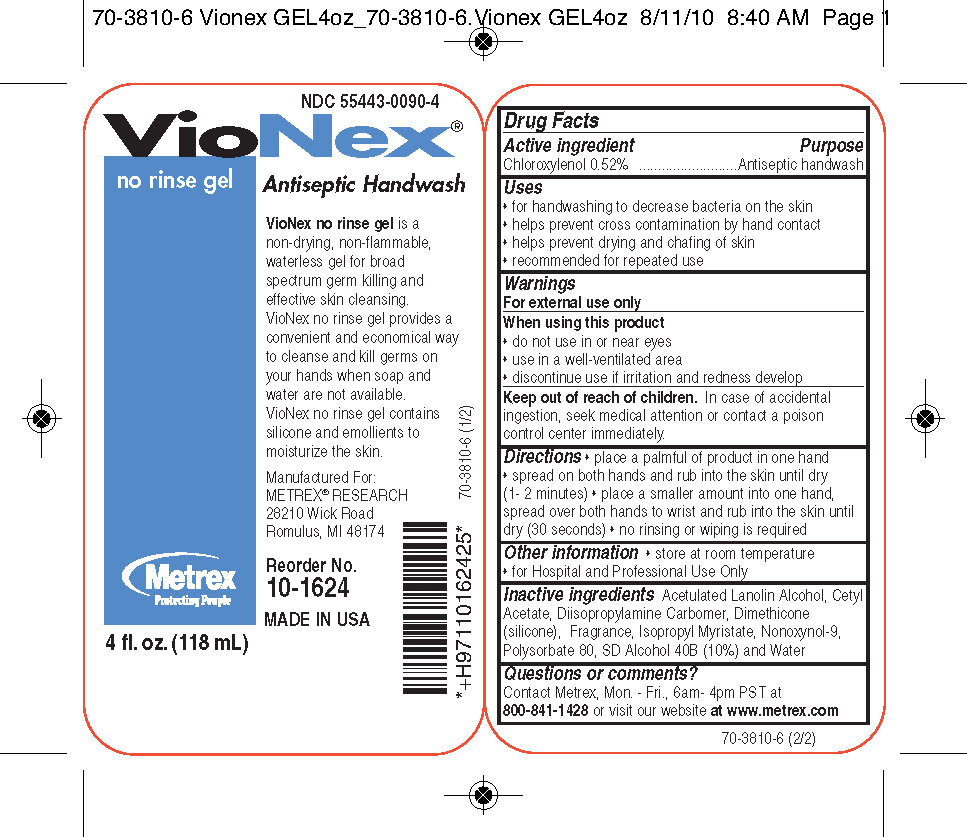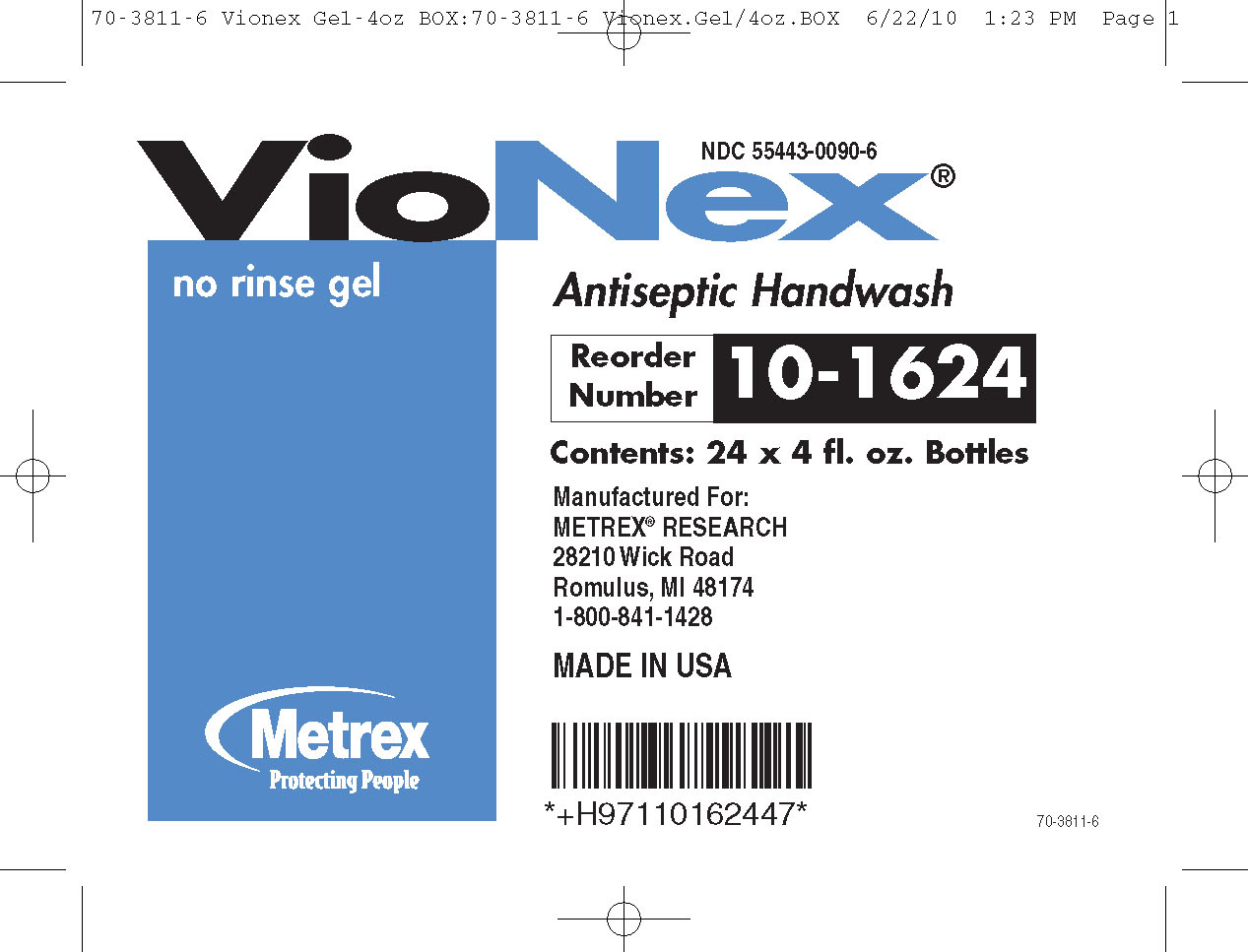 DRUG LABEL: VioNex
NDC: 55443-0090 | Form: GEL
Manufacturer: Metrex Research
Category: otc | Type: HUMAN OTC DRUG LABEL
Date: 20100817

ACTIVE INGREDIENTS: CHLOROXYLENOL 0.52 g/100 mL

VioNex no rinse gel

Principal Display Panel

VioNex
no rinse gel
Antiseptic Handwash
Manufactured for:
METREX RESEARCH
28210 Wick Road
Romulus, Michigan 48174
MADE IN USA
Reorder No.:
Metrex
Protecting People
fl. oz. (mL)

Drug Facts

Active Ingredients Purpose
Chloroxylenol 0.52%.................................Antiseptic handwash

Uses

- for handwashing to decrease bacteria on the skin
- helps prevent cross contamination by hand contact
- helps prevent drying and chafing of skin
- recommended for repeated use

Warnings

For external use only
When using this product

- do not use in or near eyes
- use in a well-ventilated area
- discontinue use if irritation and redness develop

Keep out of reach of children

In case of accidental ingestion, seek medical attention or contact a poison control center immediately.

Directions

- place a palmful of product in one hand
- spread on both hands and rub into the skin until dry (1-2 minutes)
- place a smaller amount into one hand, spread over both hands to wrist and rub into the skin until dry (30 seconds)
- no rinsing or wiping is required

Other information

- store at room temperature
- for Hospital and Professional Use Only

Inactive Ingredients

Acetulated Lanoline Alcohol, cetyl Acetate, Diisopropylamine Carbomer, Dimethicone (silicone), Fragrance, Isopropyl Myristate, Nonoxynol-9, Polysorbate 80, SD Alcohol 40B (10%) and Water

Questions or comments?

For product or technical information, contact Metrex. Monday to Friday 6am-4pm PST at 800-841-1428 or visit our web site at www.metrex.com.

INDICATIONS AND USAGE

VioNex No Rinse Gel is a non-drying, non-flammable, waterless gel for broad spectrum germ killing and effective skin cleansing.

VioNex No Rinse Gel contains silicone and emmolients to moisturize the skin.

VioNex No Rinse Gel provides a convenient and economical way to cleanse and kill germs on your hands when soap and water are not available.

PACKAGE LABEL

image of VioNexNRGBottle

image of VioNexNRGBox